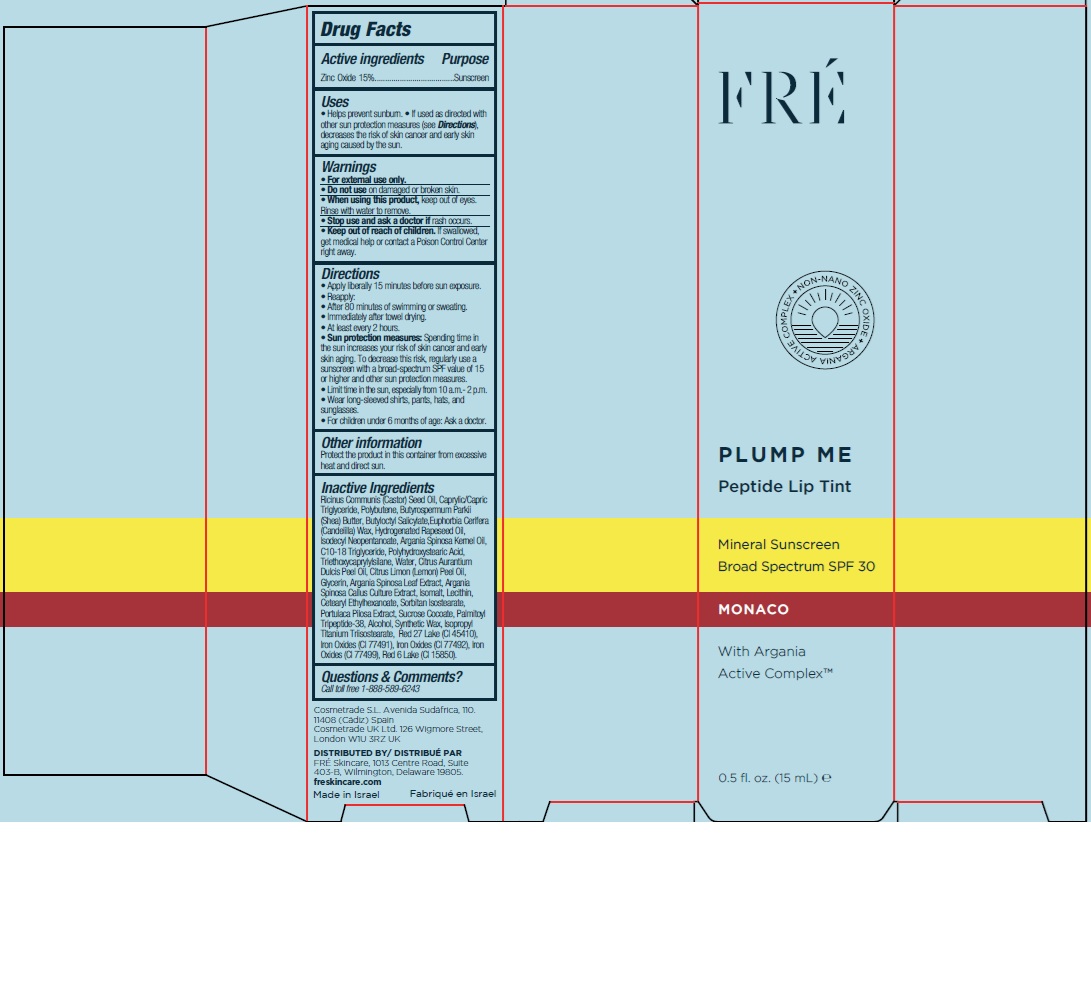 DRUG LABEL: FRE PLUMP ME PEPTIDE LIP TINT MONACO SPF 30
NDC: 69435-1409 | Form: LIQUID
Manufacturer: Peer Pharm Ltd.
Category: otc | Type: HUMAN OTC DRUG LABEL
Date: 20250130

ACTIVE INGREDIENTS: ZINC OXIDE 150 mg/1 mL
INACTIVE INGREDIENTS: ISOPROPYL TITANIUM TRIISOSTEARATE; CI 77491; CI 77492; CI 45410; LECITHIN, SUNFLOWER; ALCOHOL; GLYCERIN; ARGANIA SPINOSA LEAF; CETEARYL ETHYLHEXANOATE; CITRUS LIMON (LEMON) PEEL OIL; SHEA BUTTER; CASTOR OIL; CANDELILLA WAX; POLYHYDROXYSTEARIC ACID (2300 MW); CI 77499; CI 15850; C10-18 TRIGLYCERIDES; WATER; CITRUS AURANTIUM DULCIS (ORANGE) PEEL OIL; ARGAN OIL; PORTULACA PILOSA WHOLE; SUCROSE COCOATE; ISODECYL NEOPENTANOATE; CAPRYLIC/CAPRIC TRIGLYCERIDE; BUTYLOCTYL SALICYLATE; TRIETHOXYCAPRYLYLSILANE; SORBITAN ISOSTEARATE; SYNTHETIC WAX (1800 MW); POLYBUTENE (1400 MW); HYDROGENATED RAPESEED OIL; ISOMALT; PALMITOYL TRIPEPTIDE-38

FRE PLUMP ME PEPTIDE LIP TINT MONACO SPF 30

Active ingredients

Zinc Oxide 15%

Purpose

Sunscreen

Uses

• Helps prevent sunburn. • If used as directed with
other sun protection measures (see Directions),
decreases the risk of skin cancer and early skin
aging caused by the sun.

Warnings

• For external use only.
• Do not use on damaged or broken skin.
• When using this product, keep out of eyes.
Rinse with water to remove.

Stop use and ask a doctor

if rash occurs.

Keep out of reach of children

If swallowed,
get medical help or contact a Poison Control Center
right away.

Directions

• Apply liberally 15 minutes before sun exposure.
• Reapply:
• After 80 minutes of swimming or sweating.
• Immediately after towel drying.
• At least every 2 hours.
• Sun protection measures: Spending time in
the sun increases your risk of skin cancer and early
skin aging. To decrease this risk, regularly use a
sunscreen with a broad-spectrum SPF value of 15
or higher and other sun protection measures.
• Limit time in the sun, especially from 10 a.m.- 2 p.m.
• Wear long-sleeved shirts, pants, hats, and
sunglasses.
• For children under 6 months of age: Ask a doctor.

Other information

Protect the product in this container from excessive
heat and direct sun.

Inactive Ingredients

Ricinus Communis (Castor) Seed Oil, Caprylic/Capric
Triglyceride, Polybutene, Butyrospermum Parkii
(Shea) Butter, Butyloctyl Salicylate,Euphorbia Cerifera
(Candelilla) Wax, Hydrogenated Rapeseed Oil,
Isodecyl Neopentanoate, Argania Spinosa Kernel Oil,
C10-18 Triglyceride, Polyhydroxystearic Acid,
Triethoxycaprylylsilane, Water, Citrus Aurantium
Dulcis Peel Oil, Citrus Limon (Lemon) Peel Oil,
Glycerin, Argania Spinosa Leaf Extract, Argania
Spinosa Callus Culture Extract, Isomalt, Lecithin,
Cetearyl Ethylhexanoate, Sorbitan Isostearate,
Portulaca Pilosa Extract, Sucrose Cocoate, Palmitoyl
Tripeptide-38, Alcohol, Synthetic Wax, Isopropyl
Titanium Triisostearate, Red 27 Lake (CI 45410),
Iron Oxides (CI 77491), Iron Oxides (CI 77492), Iron
Oxides (CI 77499), Red 6 Lake (CI 15850).

Questions & Comments

Call toll free 1-888-589-6243